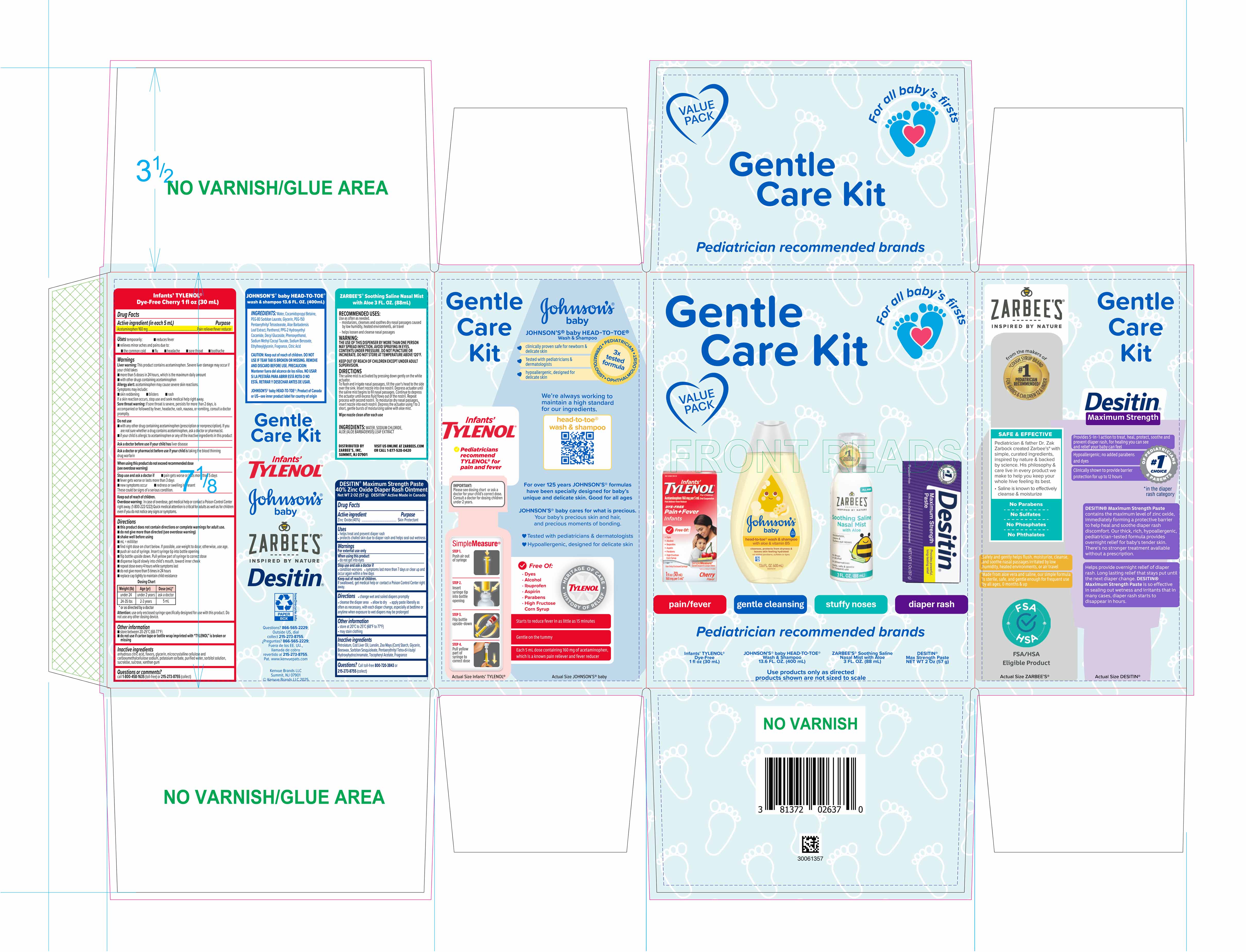 DRUG LABEL: Gentle Care Kit
NDC: 69968-0964 | Form: KIT | Route: NASAL
Manufacturer: Kenvue Brands LLC
Category: otc | Type: HUMAN OTC DRUG LABEL
Date: 20260224

ACTIVE INGREDIENTS: ACETAMINOPHEN 160 mg/5 mL; ZINC OXIDE 400 mg/1 g
INACTIVE INGREDIENTS: SORBITOL SOLUTION; ANHYDROUS CITRIC ACID; XANTHAN GUM; CARBOXYMETHYLCELLULOSE SODIUM; SUCROSE; WATER; MICROCRYSTALLINE CELLULOSE; SUCRALOSE; POTASSIUM SORBATE; GLYCERIN; PETROLATUM; LANOLIN; COD LIVER OIL; SORBITAN SESQUIOLEATE; ALPHA-TOCOPHEROL ACETATE; GLYCERIN; BEESWAX; PENTAERYTHRITYL TETRA-DI-T-BUTYL HYDROXYHYDROCINNAMATE; ZEA MAYS (CORN) STARCH

Gentle Care Kit

Desitin Diaper Rash Ointment

Drug Facts

Active ingredient

Zinc Oxide (40%)

Purpose

Skin Protectant

Uses

- helps treat and prevent diaper rash
- protects chafed skin due to diaper rash and helps seal out wetness

Warnings

For external use only.

When using this product • do not get into eyes

Stop use and ask a doctor if

• condition worsens

• symptoms last more than 7 days or clear up and occur again within a few days

Keep out of reach of children. If swallowed, get medical help or contact a Poison Control Center right away.

Directions

- change wet and soiled diapers promptly
- cleanse the diaper area
- allow to dry
- apply paste liberally as often as necessary, with each diaper change, especially at bedtime or anytime when exposure to wet diapers may be prolonged

Other information

• store at 20°C to 25°C (68°F to 77°F)

• may stain clothing

Inactive ingredients

Petrolatum, Cod Liver Oil, Lanolin, Zea Mays (Corn) Starch, Glycerin, Beeswax, Sorbitan Sesquioleate, Pentaerythrityl Tetra-di-t-butyl Hydroxyhydrocinnamate, Tocopheryl Acetate, Fragrance

Questions?

Call toll-free 800-720-3843 or 215-273-8755 (collect)

Distributed by:

Kenvue Brands LLC
Summit, NJ 07901

Infants' TYLENOL

Drug Facts

Active ingredient

Active ingredient (in each 5 mL)

Acetaminophen 160 mg

Purpose

Pain reliever/fever reducer

Uses

temporarily:

- reduces fever
- relieves minor aches and pains due to:
- the common cold ▪ flu ▪ headache ▪ sore throat ▪ toothache

Warnings

Liver warning: This product contains acetaminophen. Severe liver damage may occur if your child takes

- more than 5 doses in 24 hours, which is the maximum daily amount
- with other drugs containing acetaminophen

Allergy alert: acetaminophen may cause severe skin reactions.

Symptoms may include:

- skin reddening ▪ blisters ▪ rash

If a skin reaction occurs, stop use and seek medical help right away.

Sore throat warning: if sore throat is severe, persists for more than 2 days, is accompanied or followed by fever, headache, rash, nausea, or vomiting, consult a doctor promptly.

Do not use

▪ with any other drug containing acetaminophen (prescription or nonprescription). If you are not sure whether a drug contains acetaminophen, ask a doctor or pharmacist.

▪ if your child is allergic to acetaminophen or any of the inactive ingredients in this product

Ask a doctor before use if your child has liver disease

Ask a doctor or pharmacist before use if your child is taking the blood thinning drug warfarin

When using this product do not exceed recommended dose (see overdose warning)

Stop use and ask a doctor if

- pain gets worse or lasts more than 5 days
- fever gets worse or lasts more than 3 days
- new symptoms occur
- redness or swelling is present.

These could be signs of a serious condition.

Keep out of reach of children. Overdose warning: In case of overdose, get medical help or contact a Poison Control Center right away. (1-800-222-1222) Quick medical attention is critical for adults as well as for children even if you do not notice any signs or symptoms.

Directions

▪ this product does not contain directions or complete warnings for adult use.

▪ do not give more than directed (see overdose warning)
▪ shake well before using
▪ mL = milliliter

▪ find right dose on chart below. If possible, use weight to dose; otherwise, use age.
▪ push air out of syringe. Insert syringe tip into bottle opening
▪ flip bottle upside down. Pull yellow part of syringe to correct dose
▪ dispense liquid slowly into child’s mouth, toward inner cheek
▪ repeat dose every 4 hours while symptoms last
▪ do not give more than 5 times in 24 hours

▪ replace cap tightly to maintain child resistance

Dosing Chart

Weight (lb) | Age (yr) | Dose (mL)*
under 24 | under 2 years | ask a doctor
24-35 lbs | 2-3 years | 5

* or as directed by a doctor

Attention: use only enclosed syringe specifically designed for use with this product. Do not use any other dosing device.

Other information

▪ store between 20-25°C (68-77°F)

▪ do not use if carton tape or bottle wrap imprinted with “TYLENOL” is broken or missing

Inactive ingredients

anhydrous citric acid, flavors, glycerin, microcrystalline cellulose and carboxymethylcellulose sodium, potassium sorbate, purified water, sorbitol solution, sucralose, sucrose, xanthan gum

Questions or comments?

call 1-800-458-1635 (toll-free) or 215-273-8755 (collect)

Distributed by:

Kenvue Brands LLC

Summit, NJ 07901

PRINCIPAL DISPLAY PANEL - Kit Package

Gentle

Care Kit

For all baby’s firsts

VALUE

PACK

pain/fever

gentle cleansing

stuffy noses

diaper rash

Pediatrician recommended brands

Infants’ TYLENOL®

Dye-Free

1 fl oz (30 mL)

JOHNSON’S® baby HEAD-TO-TOE®

Wash & Shampoo

13.6 FL. OZ. (400 mL)

ZARBEE’S® Soothing Saline

Nasal Mist with Aloe

3 FL. OZ. (88 mL)

DESITIN®

Max Strength Paste

NET WT 2 Oz (57 g)

Use products only as directed

products shown are not sized to scale